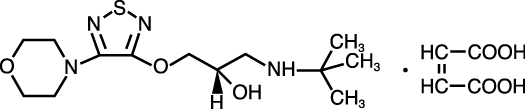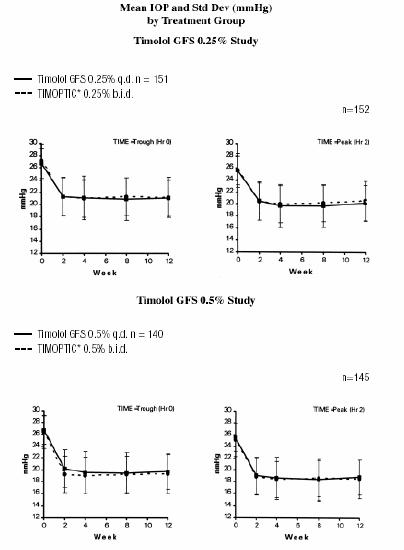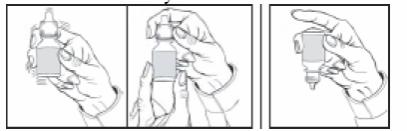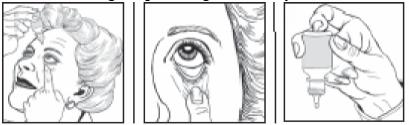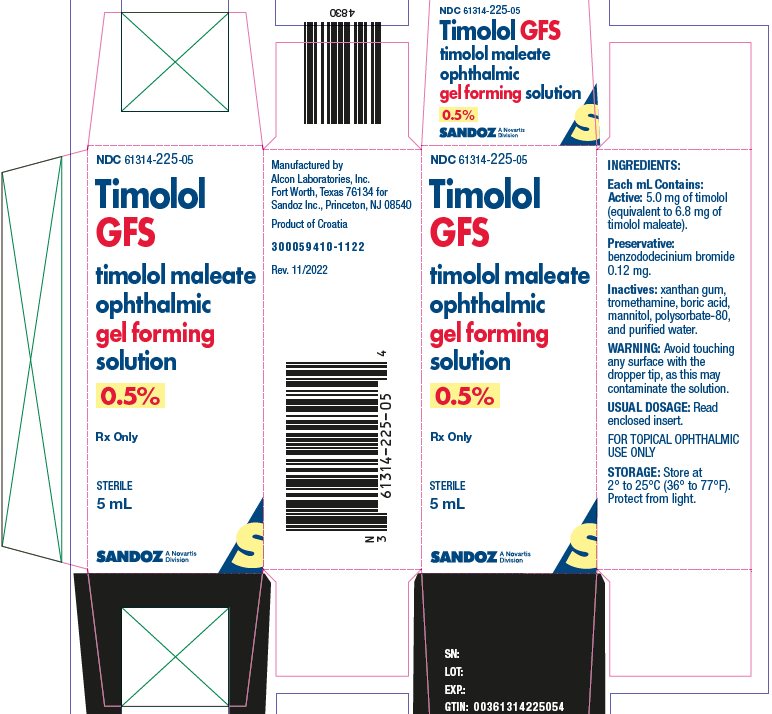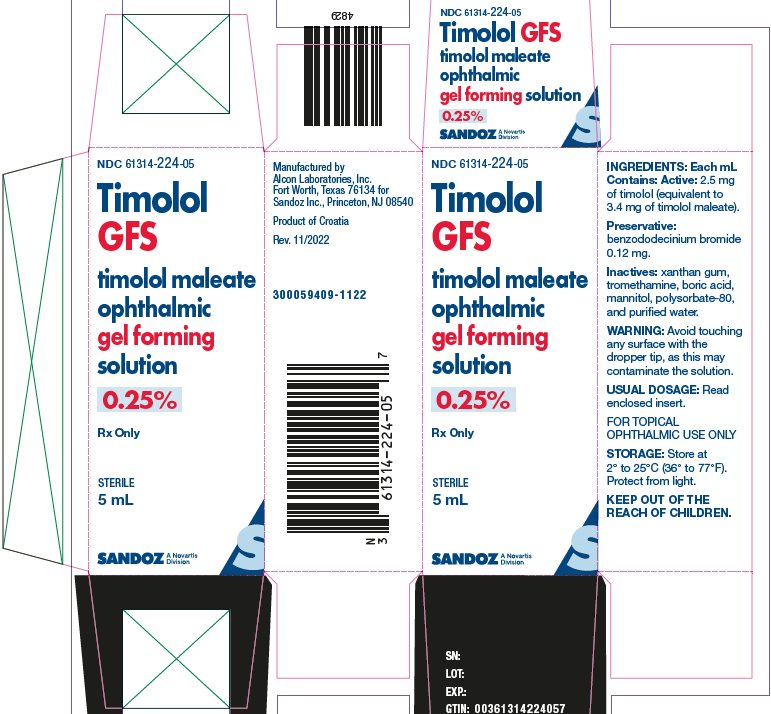 DRUG LABEL: Timolol GFS
NDC: 61314-225 | Form: SOLUTION, GEL FORMING / DROPS
Manufacturer: Sandoz Inc
Category: prescription | Type: HUMAN PRESCRIPTION DRUG LABEL
Date: 20240528

ACTIVE INGREDIENTS: TIMOLOL MALEATE 5 mg/1 mL
INACTIVE INGREDIENTS: BENZODODECINIUM BROMIDE; XANTHAN GUM; TROMETHAMINE; BORIC ACID; MANNITOL; POLYSORBATE 80; WATER

HIGHLIGHTS OF PRESCRIBING INFORMATION

These highlights do not include all the information needed to use Timolol GFS safely and effectively. See full prescribing information for Timolol GFS.
Timolol GFS (timolol maleate ophthalmic gel forming solution) 0.25% and 0.5%, for topical ophthalmic use.
Initial U.S. Approval: 1978

1 INDICATIONS AND USAGE

Timolol GFS is a beta adrenergic blocker indicated for the treatment of elevated intraocular pressure in patients with ocular hypertension or open-angle glaucoma (1).

2 DOSAGE AND ADMINISTRATION

Instill one drop in the affected eye(s) once daily (2).

3 DOSAGE FORMS AND STRENGTHS

Ophthalmic gel forming solution containing 0.25% or 0.5% of timolol (3).

4 CONTRAINDICATIONS

• Bronchial asthma (or history of) (4)

• Severe chronic obstructive pulmonary disease (4)

• Sinus bradycardia (4)

• Second or third degree atrioventricular block (4)

• Overt cardiac failure (4)

• Cardiogenic shock (4)

• Hypersensitivity to any component of this product (4)

5 WARNINGS AND PRECAUTIONS

• Same adverse reactions found with systemic administration of beta-adrenergic receptor inhibitors may occur with topical ophthalmic administration (5.1).

• Beta-adrenergic receptor inhibitors may mask signs and symptoms of hypoglycemia and should be administered with caution in diabetic patients subject to hypoglycemia (5.5).

• Beta-adrenergic receptor inhibitors may mask certain clinical signs (e.g. tachycardia) of hyperthyroidism (5.6).

6 ADVERSE REACTIONS

Most common adverse reactions (1% to 5%) occur upon instillation and include transient blurred vision, burning, and stinging (6.1).

To report SUSPECTED ADVERSE REACTIONS, contact Sandoz Inc. at 1-800-525-8747 or FDA at 1-800-FDA-1088 or www.fda.gov/medwatch.

7 DRUG INTERACTIONS

• Oral beta-adrenergic receptor inhibitors may have additive effects (7.1)

• Digitalis and calcium antagonists may have additive effects (7.2)

• Catecholamine-depleting drugs may have additive effects (7.3)

• Quinidine may have additive effects (7.4)

FULL PRESCRIBING INFORMATION

1 INDICATIONS AND USAGE

Timolol GFS 0.25% and 0.5% are indicated for the treatment of elevated intraocular pressure in patients with ocular hypertension or open-angle glaucoma.

2 DOSAGE AND ADMINISTRATION

Instill one drop of Timolol GFS (either 0.25% or 0.5%) in the affected eye(s) once daily. Shake once before each use.

Timolol GFS may be used alone or in combination with other intraocular pressure lowering medications. Concomitant topical ophthalmic medications should be administered at least 10 minutes before instilling Timolol GFS.

3 DOSAGE FORMS AND STRENGTHS

Ophthalmic gel forming solution: slightly opalescent, colorless to nearly colorless solution containing 0.25% or 0.5% of timolol.

Available in 5 mL size bottle filled with 2.5 mL or 5 mL solution.

4 CONTRAINDICATIONS

Timolol GFS is contraindicated in patients with:

• bronchial asthma

• history of bronchial asthma

• severe chronic obstructive pulmonary disease

• sinus bradycardia

• second or third degree atrioventricular block

• overt cardiac failure

• cardiogenic shock

• hypersensitivity to any component of this product.

5 WARNINGS AND PRECAUTIONS

5.1 Systemic Absorption

As with many topically applied ophthalmic drugs, Timolol GFS is absorbed systemically.

The same adverse reactions found with systemic administration of beta-adrenergic receptor inhibitors may occur with topical ophthalmic administration. For example, severe respiratory reactions and cardiac reactions, including death due to bronchospasm in patients with asthma, and death due to cardiac failure, have been reported following systemic or ophthalmic administration of timolol maleate [see Contraindications (4)].

5.2 Cardiac Failure

Sympathetic stimulation may be essential for support of the circulation in individuals with diminished myocardial contractility, and its inhibition by beta-adrenergic receptor blockade may precipitate more severe failure.

In patients without a history of cardiac failure, continued depression of the myocardium with beta-adrenergic receptor inhibitors over a period of time can, in some cases, lead to cardiac failure. At the first sign or symptom of cardiac failure, Timolol GFS should be discontinued.

5.3 Bronchospasm and Obstructive Pulmonary Disease

Bronchospasm may occur. Patients with chronic obstructive pulmonary disease (e.g., chronic bronchitis, emphysema) of mild or moderate severity, bronchospastic disease, or a history of bronchospastic disease (other than bronchial asthma or a history of bronchial asthma, in which Timolol GFS is contraindicated [see Contraindications (4)]) should, in general, not receive beta-adrenergic receptor inhibitors, including Timolol GFS.

5.4 Surgical Anesthesia

The necessity or desirability of withdrawal of beta-adrenergic receptor inhibitors prior to major surgery is controversial. Beta-adrenergic receptor blockade impairs the ability of the heart to respond to beta-adrenergically mediated reflex stimuli. This may augment the risk of general anesthesia in surgical procedures. Some patients receiving beta-adrenergic receptor inhibitors have experienced protracted, severe hypotension during anesthesia. Difficulty in restarting and maintaining the heartbeat has also been reported. In patients undergoing elective surgery, consider gradual withdrawal of beta-adrenergic receptor inhibitors. If necessary during surgery, the effects of beta-adrenergic receptor inhibitors may be reversed by sufficient doses of adrenergic agonists.

5.5 Diabetes Mellitus

Beta-adrenergic receptor inhibitors should be administered with caution in diabetic patients subject to hypoglycemia who are receiving insulin or oral hypoglycemic agents. Beta-adrenergic receptor inhibitors may mask the signs and symptoms of acute hypoglycemia.

5.6 Thyrotoxicosis

Beta-adrenergic receptor inhibitors may mask certain clinical signs (e.g. tachycardia) of hyperthyroidism. Patients suspected of developing thyrotoxicosis should be managed carefully to avoid abrupt withdrawal of beta-adrenergic receptor inhibitors that might precipitate a thyroid storm.

5.7 Cerebrovascular Insufficiency

Because of potential effects of beta-adrenergic receptor inhibitors on blood pressure and pulse, these agents should be used with caution in patients with cerebrovascular insufficiency. If signs or symptoms suggesting reduced cerebral blood flow develop following initiation of therapy with Timolol GFS, alternative therapy should be considered.

5.8 Bacterial Keratitis

Bacterial keratitis may occur with use of multiple dose containers of topical ophthalmic products when these containers are inadvertently contaminated by patients who, in most cases, had a concurrent corneal disease or a disruption of the ocular epithelial surface. Instruct patients on appropriate instillation techniques [see Patient Counseling Information (17)].

5.9 Choroidal Detachment

Choroidal detachment after filtration procedures has been reported with the administration of aqueous suppressant (e.g., timolol) therapy.

5.10 Angle-Closure Glaucoma

In patients with angle-closure glaucoma, the immediate objective of treatment is to reopen the angle. This may require constricting the pupil. Timolol GFS has little or no effect on the pupil and should not be used alone in the treatment of angle-closure glaucoma.

5.11 Atopy/Anaphylaxis

While taking beta receptor inhibitors, patients with a history of atopy or a history of severe anaphylactic reactions to a variety of allergens may be more reactive to repeated accidental, diagnostic, or therapeutic challenge with such allergens. Such patients may be unresponsive to the usual doses of epinephrine used to treat anaphylactic reactions.

5.12 Muscle Weakness

Beta-adrenergic blockade has been reported to potentiate muscle weakness consistent with certain myasthenic symptoms (e.g., diplopia, ptosis, and generalized weakness). Timolol has been reported to increase muscle weakness in some patients with myasthenia gravis or myasthenic symptoms.

6 ADVERSE REACTIONS

6.1 Clinical Trials Experience

Because clinical trials are conducted under widely varying conditions, adverse reaction rates observed in the clinical trials of a drug cannot be directly compared to rates in the clinical trials of another drug and may not reflect the rates observed in practice.

In clinical trials with Timolol GFS, transient blurred vision upon instillation of the drop was reported in approximately one in three patients. The frequency of patients reporting burning and stinging upon instillation was approximately one in eight patients which was comparable to that observed for TIMOPTIC*.

Adverse reactions reported in 1% to 5% of patients were:

Ocular: Blepharitis, conjunctivitis, crusting, discomfort, foreign body sensation, hyperemia, pruritus and tearing;

Systemic: Headache, hypertension, and upper respiratory infections.

In a 3-month, double-masked, active-controlled, multicenter study in pediatric patients, the adverse reactions profile of Timolol GFS 0.25% and 0.5% was comparable to that seen in adult patients.

6.2 Additional Potential Adverse Reactions Associated with Timolol Maleate

The following additional adverse experiences have been reported with the ocular administration of this or other timolol maleate formulations:

BODY AS A WHOLE

Asthenia/fatigue and chest pain.

CARDIOVASCULAR

Bradycardia, arrhythmia, hypotension, hypertension, syncope, heart block, cerebral vascular accident, cerebral ischemia, cardiac failure, worsening of angina pectoris, palpitation, cardiac arrest, pulmonary edema, dizziness, edema, claudication, Raynaud's phenomenon, and cold hands and feet.

DIGESTIVE

Nausea, diarrhea, dyspepsia, anorexia, and dry mouth.

IMMUNOLOGIC

Systemic lupus erythematosus.

NERVOUS SYSTEM/PSYCHIATRIC

Increase in signs and symptoms of myasthenia gravis, paresthesia, somnolence, insomnia, nightmares, behavioral changes and psychic disturbances including confusion, hallucinations, anxiety, depression, disorientation, nervousness, and memory loss.

SKIN

Alopecia and psoriasiform rash or exacerbation of psoriasis.

HYPERSENSITIVITY

Signs and symptoms of systemic allergic reactions, including anaphylaxis, angioedema, urticaria and localized and generalized rash.

RESPIRATORY

Bronchospasm (predominantly in patients with pre-existing bronchospastic disease), respiratory failure, dyspnea, nasal congestion, and cough.

ENDOCRINE

Masked symptoms of hypoglycemia in diabetic patients [see Warnings and Precautions (5.5)].

SPECIAL SENSES

Signs and symptoms of ocular irritation including blepharitis, keratitis, and dry eyes; ptosis; decreased corneal sensitivity; cystoid macular edema; visual disturbances including refractive changes and diplopia; pseudopemphigoid; choroidal detachment following filtration surgery [see Warnings and Precautions (5.9)]; and tinnitus.

UROGENITAL

Retroperitoneal fibrosis, decreased libido, impotence and Peyronie's disease.

7 DRUG INTERACTIONS

7.1 Oral Beta-Adrenergic Receptor Inhibitors

Patients who are receiving a beta-adrenergic receptor inhibiting agent orally and Timolol GFS should be observed for potential additive effects of beta-blockade, both systemic and on intraocular pressure. Patients should not usually receive two topical ophthalmic beta-adrenergic receptor inhibiting agents concurrently.

7.2 Digitalis and Calcium Antagonists

The concomitant use of beta-adrenergic receptor inhibiting agents with digitalis and calcium antagonists may have additive effects in prolonging atrioventricular conduction time.

Caution should be used in the co-administration of beta-adrenergic receptor inhibitors, such as Timolol GFS, and oral or intravenous calcium antagonists because of possible atrioventricular conduction disturbances, left ventricular failure, or hypotension. In patients with impaired cardiac function, co-administration should be avoided.

7.3 Catecholamine-Depleting Drugs

Close observation of the patient is recommended when a beta receptor inhibitor is administered to patients receiving catecholamine-depleting drugs such as reserpine, because of possible additive effects and the production of hypotension and/or marked bradycardia, which may result in vertigo, syncope, or postural hypotension.

7.4 Quinidine

Potentiated systemic beta-blockade (e.g., decreased heart rate) has been reported during combined treatment with quinidine and timolol, possibly because quinidine inhibits the metabolism of timolol via the P-450 enzyme, CYP2D6.

7.5 Clonidine

Oral beta-adrenergic receptor inhibiting agents may exacerbate the rebound hypertension which can follow the withdrawal of clonidine. There have been no reports of exacerbation of rebound hypertension with ophthalmic timolol maleate.

7.6 Injectable Epinephrine

Patients may be unresponsive to the usual doses of epinephrine used to treat anaphylactic reactions.[See Warnings and Precautions (5.11)]

8 USE IN SPECIFIC POPULATIONS

8.1 Pregnancy

Risk Summary

There are no adequate and well-controlled studies in pregnant women with timolol maleate to inform a drug-associated risk. Administration of oral timolol maleate to pregnant mice, rats and rabbits did not produce teratogenicity at clinically relevant systemic exposures (see Data). Because animal reproductive studies are not always predictive of human response, Timolol GFS should be used during pregnancy only if the potential benefit justifies the potential risk to the fetus.

In the U.S. general population, the estimated background risk of major birth defects and miscarriage in clinically recognized pregnancies is 2-4% and 15-20%, respectively.

Data

Animal Data

Teratogenicity studies with timolol in mice, rats, and rabbits at oral doses up to 50 mg/kg/day (7,000 times the systemic exposure following the maximum recommended human ophthalmic dose) demonstrated no evidence of fetal malformations. Although delayed fetal ossification was observed at this dose in rats, there were no adverse effects on postnatal development of offspring. Doses of 1,000 mg/kg/day (142,000 times the systemic exposure following the maximum recommended human ophthalmic dose) were maternotoxic in mice and resulted in an increased number of fetal resorptions. Increased fetal resorptions were also seen in rabbits at doses of 14,000 times the systemic exposure following the maximum recommended human ophthalmic dose, in this case without apparent maternotoxicity.

8.2 Lactation

Risk Summary

Timolol maleate has been detected in human milk following oral and ophthalmic drug administration. The developmental and health benefits of breastfeeding should be considered along with the mother’s clinical need for Timolol GFS and any potential adverse effects on the breastfed child from Timolol GFS.

8.4 Pediatric Use

The safety and IOP-lowering effect of Timolol GFS 0.25% and 0.5% have been demonstrated in pediatric patients in a 3-month, multicenter, double-masked, active-controlled trial.

8.5 Geriatric Use

No overall differences in safety or effectiveness have been observed between elderly and younger patients.

10 OVERDOSAGE

No data are available with regard to human overdose with, or accidental oral ingestion of Timolol GFS. There have been reports of inadvertent overdose with Timolol maleate ophthalmic solution resulting in systemic effects similar to those seen with systemic beta-adrenergic receptor inhibitors such as dizziness, headache, shortness of breath, bradycardia, bronchospasm, and cardiac arrest [see also Adverse Reactions (6)].

Overdosage has been reported with timolol maleate tablets. A 30-year old female ingested 650 mg of timolol maleate tablets (maximum recommended oral daily dose is 60 mg) and experienced second and third degree heart block. She recovered without treatment but approximately two months later developed irregular heartbeat, hypertension, dizziness, tinnitus, faintness, increased pulse rate, and borderline first degree heart block.

An in vitro hemodialysis study, using ^14C timolol added to human plasma or whole blood, showed that timolol was readily dialyzed from these fluids; however, a study of patients with renal failure showed that timolol did not dialyze readily.

11 DESCRIPTION

Timolol GFS (timolol maleate ophthalmic gel forming solution) is a non-selective beta-adrenergic receptor inhibitor. Its chemical name is (-)-1-(tert-butylamino)-3-[(4-morpholino-1,2,5-thia diazol-3-yl)oxy]-2-propanol maleate (1:1) (salt).

Timolol maleate possesses an asymmetric carbon atom in its structure and is provided at the levo-isomer. The nominal optical rotation of timolol maleate is:

[α] 25° in 0.1N HCl (C=5%) = -12.2°

405 nm

Its molecular formula is C13H24N4O3S·C4H4O4 and its structural formula is:

Timolol maleate has a molecular weight of 432.50. It is a white, odorless, crystalline powder which is soluble in water, methanol, and alcohol. Timolol GFS is a colorless to nearly colorless, slightly opalescent, and slightly viscous, is supplied as a sterile, isotonic, buffered, aqueous topical ophthalmic solution of timolol maleate in two dosage strengths. Timolol GFS has a pH of approximately 6.9 and an osmolality of approximately 290 mOsmol/kg. Each mL of Timolol GFS 0.25% contains 2.5 mg of timolol (3.4 mg of timolol maleate). Each mL of Timolol GFS 0.5% contains 5 mg of timolol (6.8 mg of timolol maleate). Inactive ingredients: boric acid, mannitol, polysorbate-80, tromethamine, xanthan gum, and purified water. Preservative: benzododecinium bromide 0.012%.

Xanthan gum is a purified high molecular weight polysaccharide gum produced from the fermentation by bacterium Xanthomonas campestris. An aqueous solution of xanthan gum, in the presence of tear protein (lysozyme), forms a gel. Upon contact with the precorneal tear film, Timolol GFS forms a gel that is subsequently removed by the flow of tears.

12 CLINICAL PHARMACOLOGY

12.1 Mechanism of Action

Timolol maleate is a beta1 and beta2 (non-selective) adrenergic receptor inhibitor that does not have significant intrinsic sympathomimetic, direct myocardial depressant, or local anesthetic (membrane-stabilizing) activity. Timolol GFS, when applied topically to the eye, has the action of reducing elevated, as well as normal, intraocular pressure, whether or not accompanied by glaucoma. Elevated intraocular pressure is a major risk factor in the pathogenesis of glaucomatous visual field loss and optic nerve damage. The precise mechanism of the ocular hypotensive action of Timolol GFS is not clearly established at this time. Tonography and fluorophotometry studies of Timolol GFS in man suggest that its predominant action may be related to reduced aqueous formation. However, in some studies, a slight increase in outflow facility was also observed. Beta-adrenergic receptor blockade reduces cardiac output in both healthy subjects and patients with heart disease. In patients with severe impairment of myocardial function beta-adrenergic receptor inhibitors may inhibit the stimulatory effect of the sympathetic nervous system necessary to maintain adequate cardiac function. Beta-adrenergic receptor blockade in the bronchi and bronchioles results in increased airway resistance from unopposed parasympathetic activities. Such an effect in patients with asthma or other bronchospastic conditions is potentially dangerous.

12.2 Pharmacodynamics

Because in some patients the intraocular pressure-lowering response to Timolol GFS may require a few weeks to stabilize, evaluation should include a determination of intraocular pressure after approximately 4 weeks of treatment with Timolol GFS. If the patient's intraocular pressure is still not at a satisfactory level on this regimen, concomitant therapy can be considered.

12.3 Pharmacokinetics

Following topical ocular administration of timolol to humans, low concentrations of drug are found in plasma. After bilateral administration of a 0.5% timolol maleate solution to healthy volunteers, maximum plasma concentrations were generally below 5 ng/mL. Dosages higher than one drop of 0.5% Timolol GFS once daily have not been studied.

Pharmacokinetic studies in humans using this gel forming solution formulation were not performed. However, systemic uptake from a gel matrix is expected to be slower than from a non-gel forming solution based on studies using other gel forming solutions. The maximum plasma timolol concentration from the gel forming drop is not expected to exceed those of the 0.5% timolol maleate solution.

13 NONCLINICAL TOXICOLOGY

13.1 Carcinogenesis, Mutagenesis, Impairment of Fertility

Carcinogenesis

In a two-year study of timolol maleate administered orally to rats, there was a statistically significant increase in the incidence of adrenal pheochromocytomas in male rats administered 300 mg/kg/day (approximately 42,000 times the systemic exposure following the maximum recommended human ophthalmic dose). Similar differences were not observed in rats administered oral doses equivalent to approximately 14,000 times the maximum recommended human ophthalmic dose. In a lifetime oral study in mice, there were statistically significant increases in the incidence of benign and malignant pulmonary tumors, benign uterine polyps, and mammary adenocarcinomas in female mice at 500 mg/kg/day (approximately 71,000 times the systemic exposure following the maximum recommended human ophthalmic dose), but not at 5 or 50 mg/kg/day (approximately 700 or 7,000, respectively, times the systemic exposure following the maximum recommended human ophthalmic dose). In a subsequent study in female mice, in which postmortem examinations were limited to the uterus and the lungs, a statistically significant increase in the incidence of pulmonary tumors was again observed at 500 mg/kg/day. The increased occurrence of mammary adenocarcinomas was associated with elevations in serum prolactin, which occurred in female mice administered oral timolol at 500 mg/kg/day, but not at oral doses of 5 or 50 mg/kg/day. An increased incidence of mammary adenocarcinomas in rodents has been associated with administration of several other therapeutic agents that elevate serum prolactin, but no correlation between serum prolactin levels and mammary tumors has been established in humans. Furthermore, in adult human female subjects who received oral dosages of up to 60 mg of timolol maleate (the maximum recommended human oral dosage), there were no clinically meaningful changes in serum prolactin.

Mutagenesis

Timolol maleate was devoid of mutagenic potential when tested in vivo (mouse) in the micronucleus test and cytogenetic assay (doses up to 800 mg) and in vitro in a neoplastic cell transformation assay (up to 100 mcg/mL). In Ames tests, the highest concentrations of timolol employed, 5,000 or 10,000 mcg/plate, were associated with statistically significant elevations of revertants observed with tester strain TA 100 (in seven replicate assays), but not in the remaining three strains. In the assays with tester strain TA 100, no consistent dose-response relationship was observed, and the ratio of test to control revertants did not reach 2. A ratio of 2 is usually considered the criterion for a positive Ames test.

Impairment of Fertility

Reproduction and fertility studies in rats demonstrated no adverse effect on male or female fertility at doses up to 21,000 times the systemic exposure following the maximum recommended human ophthalmic dose.

14 CLINICAL STUDIES

In controlled, double-masked, multicenter clinical studies, Timolol GFS administered once daily was compared to equivalent concentrations of TIMOPTIC* (timolol maleate ophthalmic solution) administered twice daily. Timolol GFS once daily was shown to be equally effective in lowering intraocular pressure as the equivalent concentration of TIMOPTIC administered twice daily.

The effect of timolol in lowering intraocular pressure was evident for 24 hours with a single dose of Timolol GFS. Repeated observations over a three-month study period indicate that the intraocular pressure-lowering effect of Timolol GFS was consistent. The results from the clinical trials are shown in the following figures.

Timolol GFS administered once daily had a safety profile similar to that of an equivalent concentration of TIMOPTIC administered twice daily. Due to the physical characteristics of the formulation, transient blurred vision was reported more frequently in patients administered Timolol GFS [see Adverse Reactions (6)]. Timolol GFS has not been studied in patients wearing contact lenses.

16 HOW SUPPLIED/STORAGE AND HANDLING

Timolol GFS (timolol maleate ophthalmic gel forming solution) 0.25% and 0.5%, are both supplied as either a 2.5 mL or 5 mL slightly opalescent, colorless to nearly colorless solution in a 5 mL white polyethylene bottle with a natural polyethylene dropper tip and a yellow polypropylene overcap. Tamper evidence is provided with a shrink band around the closure and neck area of the bottle.

• 0.25% 2.5 mL fill NDC 61314-224-25

5 mL fill NDC 61314-224-05

• 0.5% 2.5 mL fill NDC 61314-225-25

5 mL fill NDC 61314-225-05

Storage and Handling

Store at 2°C to 25°C (36°F to 77°F). After opening, Timolol GFS can be used until the expiration date on the bottle.

Protect from light.

17 PATIENT COUNSELING INFORMATION

How to Use the Timolol GFS solution?

The bottle is designed to assure the delivery of a precise dose of medication. Before using your bottle, read the complete instructions carefully.

1. If you use other topically applied ophthalmic medications, they should be administered at least 10 minutes before Timolol GFS.

2. Wash hands before each use.

3. Before using the medication for the first time, be sure the Safety Seal on the bottle is unbroken.

4. Tear off the Safety Seal to break the seal.

5. Before each use, shake once and remove the screw cap.

6. Invert the bottle and hold the bottle between your thumb and middle finger, with the tips of the fingers pointing towards you.

7. Tilt your head back and position the bottle above the affected eye. DO NOT TOUCH THE EYE WITH THE TIP OF THE DROPPER.

8. With the opposite hand, place a finger under the eye. Gently pull down until a "V" pocket is made between your eye and lower lid.

9. With the hand holding the bottle, place your index finger on the bottom of the bottle. Push the bottom of the bottle to dispense one drop of medication. DO NOT SQUEEZE THE SIDES OF THE BOTTLE.

10. Repeat 6, 7, 8, and 9 with other eye if instructed to do so.

11. Replace screw cap by turning until firmly touching the bottle.

Avoiding Contamination of the Product

Instruct patients to avoid allowing the tip of the dispensing container to contact the eye(s) or surrounding structures. Advise patients that ocular solutions, if handled improperly, could become contaminated by common bacteria known to cause ocular infections. Serious damage to the eye(s) and subsequent loss of vision may result from using contaminated solutions [see Warnings and Precautions (5.8)].

When to Seek Physician Advice

Advise patients that if they have ocular surgery or develop an intercurrent ocular condition (e.g., trauma or infection), they should immediately seek their physician's advice concerning the continued use of the present multidose container.

Administration Instructions

Instruct patients to invert the closed container and shake once before each use. It is not necessary to shake the container more than once.

Instruct patients requiring concomitant topical ophthalmic medications to administer these at least 10 minutes before instilling Timolol GFS.

Asthma, COPD, Sinus Bradycardia, AV Block, Cardiac Failure, Cardiogenic Shock

Advise patients with bronchial asthma, a history of bronchial asthma, severe chronic obstructive pulmonary disease, sinus bradycardia, second or third degree atrioventricular block, or cardiac failure to not use Timolol GFS [see Contraindications (4)].

Temporary Blurred Vision

Advise patients that transient blurred vision or visual disturbance, generally lasting from 30 seconds to 5 minutes, following instillation may impair the ability to perform hazardous tasks such as operating machinery or driving a motor vehicle.

*TIMOPTIC is a Registered trademark of Merck & Co., Inc.

Manufactured by:

Alcon Laboratories, Inc.

Fort Worth, Texas 76134 for

Sandoz Inc.

Princeton, NJ 08540

300066885-0524

PACKAGE/LABEL PRINCIPAL DISPLAY PANEL

Fdgdfgdf

Package/Label Display Panel

Vfdgvdfsg